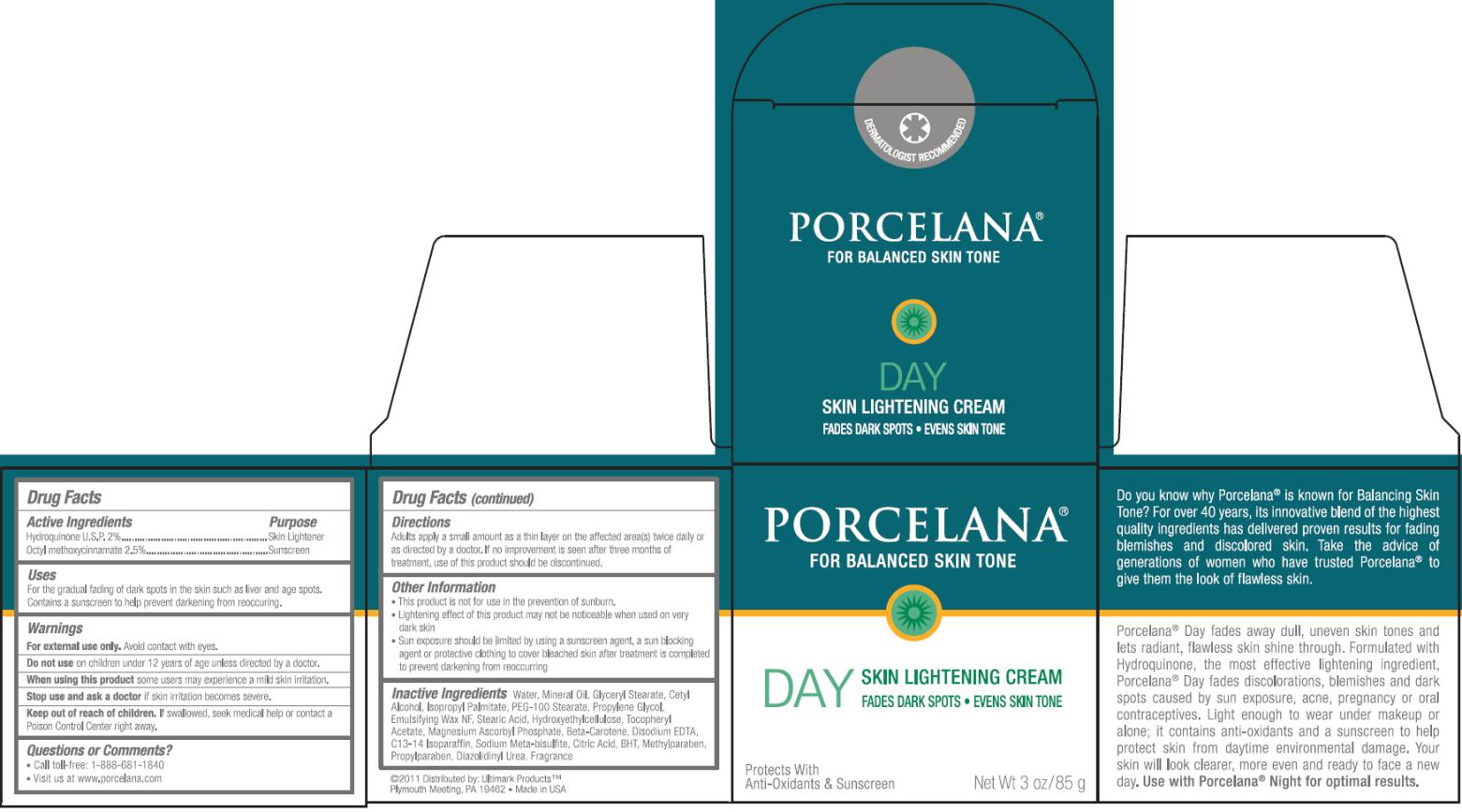 DRUG LABEL: Porcelana Day Skin Lightening
NDC: 51545-110 | Form: CREAM
Manufacturer: Ultimark Products LLC
Category: otc | Type: HUMAN OTC DRUG LABEL
Date: 20171214

ACTIVE INGREDIENTS: HYDROQUINONE 0.02 g/1 g; OCTINOXATE 0.025 g/1 g
INACTIVE INGREDIENTS: WATER; MINERAL OIL; GLYCERYL MONOSTEARATE; CETYL ALCOHOL; ISOPROPYL PALMITATE; PEG-100 STEARATE; PROPYLENE GLYCOL; STEARIC ACID; .ALPHA.-TOCOPHEROL ACETATE; MAGNESIUM ASCORBYL PHOSPHATE; .BETA.-CAROTENE; EDETATE DISODIUM; C13-14 ISOPARAFFIN; SODIUM METABISULFITE; CITRIC ACID MONOHYDRATE; BUTYLATED HYDROXYTOLUENE; METHYLPARABEN; PROPYLPARABEN; DIAZOLIDINYL UREA

Porcelana Day Skin Lightening Cream

Active Ingredient

Hydroquinone U.S.P. 2%

Purpose

Skin Lightener

Active Ingredient

Octinoxate 2.5%

Purpose

Sunscreen

Uses:

- Lightens dark spots, blemishes, freckles and discolorations of the skin caused by sun exposure, age, acne, pregnancy and the use of oral contraceptives.
- Contains a sunscreen to keep darkening from reoccurring.

Warnings

For External use only. Avoid contact with eyes. Some users of this product may experience a mild skin irritation. If skin irritation becomes severe, stop use and consult a doctor.

Do Not use on

children under 12 years of age unless directed by a doctor.

Keep out of the reach of children.

If swallowed, get medical help or contact a Poison Control Center right away. If pregnant or breast-feeding, ask a doctor before use.

Questions or Comments?

Call 1-800-820-8717

Monday - Friday 9:00 - 6:00 EST or visit us at: www.nicenebrands.com

¿Las Preguntas o Comentarios? Llame al 1-800-820-8717

Lunes - Viernes 9:00 - 6:00 EST, o visítenos en:

www.nicenebrands.com

Directions

- Adults: Apply a small amount as a thin layer on the affected area twice daily, or use as directed by a doctor. If no improvement is seen after 3 months of treatment, use of this product should be discontinued.
- Lightening effect of this product may not be noticeable when used on very dark skin.
- Children under 12 years of age: do not use unless directed by a doctor
- Sun exposure should be limited by using a sunscreen agent, a sun blocking agent, or protective clothing to cover bleached skin after treatment is completed in order to prevent darkening from reoccurring.

Inactive Ingredients

Water, Mineral Oil, Glyceryl Stearate, Cetyl Alcohol, Isopropyl Palmitate, PEG-100 Stearate, Propylene Glycol, Emulsifying Wax NF, Stearic Acid, Hydroxyethylcellulose, Tocopheryl Acetate, Magnesium Ascorbyl Phosphate, Beta-Carotene, Disodium EDTA, C13-14 Isoparaffin, Sodium Meta-Bisulfite, Citric Acid, BHT, Methylparaben, Propylparaben, Diazolidinyl Urea, Fragrance.

PRINCIPAL DISPLAY PANEL

PORCELANA®
FOR BALANCED SKIN TONE
DAY
SKIN LIGHTENING CREAM
FADES DARK SPOTS EVENS SKIN TONE
Protects With
Anti-Oxidants & Sunscreen Net Wt 3 oz/85 g